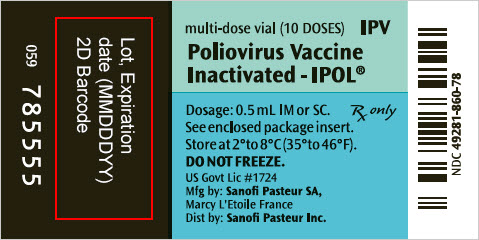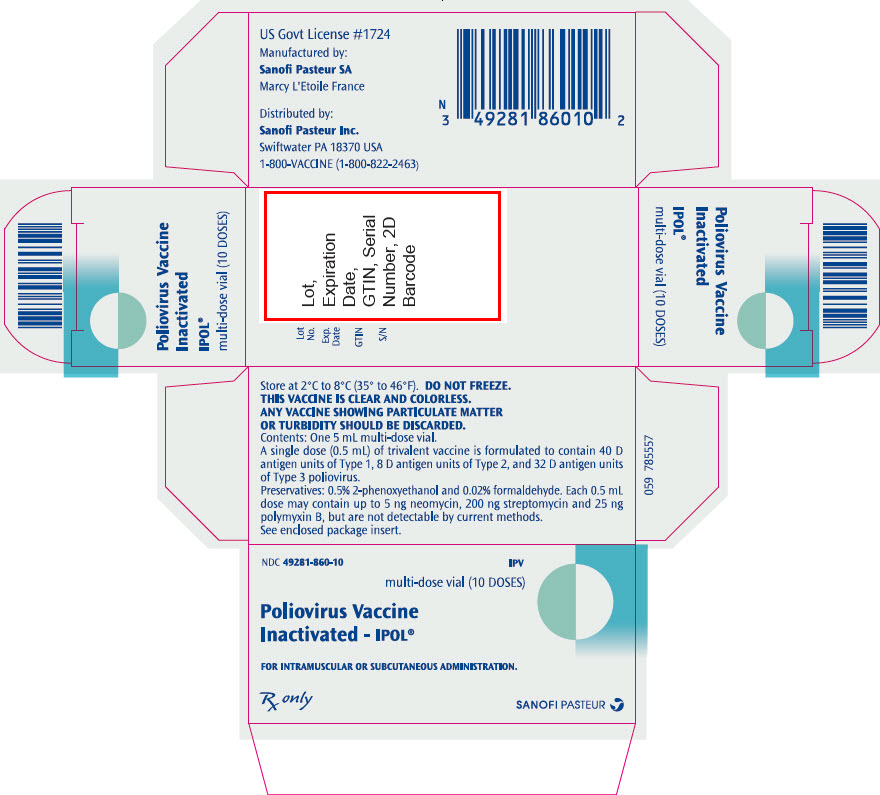 DRUG LABEL: IPOL
NDC: 49281-860 | Form: INJECTION, SUSPENSION
Manufacturer: Sanofi Pasteur Inc.
Category: other | Type: VACCINE LABEL
Date: 20260130

ACTIVE INGREDIENTS: POLIOVIRUS TYPE 1 ANTIGEN (FORMALDEHYDE INACTIVATED) 40 [D'ag'U]/0.5 mL; POLIOVIRUS TYPE 2 ANTIGEN (FORMALDEHYDE INACTIVATED) 8 [D'ag'U]/0.5 mL; POLIOVIRUS TYPE 3 ANTIGEN (FORMALDEHYDE INACTIVATED) 32 [D'ag'U]/0.5 mL
INACTIVE INGREDIENTS: PHENOXYETHANOL 3 uL/0.5 mL; FORMALDEHYDE 20 ug/0.5 mL; NEOMYCIN 5 ng/0.5 mL; STREPTOMYCIN 200 ng/0.5 mL; POLYMYXIN B 25 ng/0.5 mL

Poliovirus Vaccine Inactivated
IPOL®

AHFS Category: 80:12 IPV

Rx only

DESCRIPTION

IPOL®, Poliovirus Vaccine Inactivated, produced by Sanofi Winthrop Industrie , is a sterile suspension of three types of poliovirus: Type 1 (Mahoney), Type 2 (MEF-1), and Type 3 (Saukett). IPOL vaccine is a highly purified, inactivated poliovirus vaccine with enhanced potency. Each of the three strains of poliovirus is individually grown in vero cells, a continuous line of monkey kidney cells cultivated on microcarriers. (1) (2) The cells are grown in Eagle MEM modified medium, supplemented with newborn calf bovine serum tested for adventitious agents prior to use, originated from countries free of bovine spongiform encephalopathy. For viral growth, the culture medium is replaced by M-199, without calf bovine serum. This culture technique and improvements in purification, concentration, and standardization of poliovirus antigen produce a more potent and consistent immunogenic vaccine than the inactivated poliovirus vaccine (IPV) available in the US prior to 1988. (3) (4)

After clarification and filtration, viral suspensions are concentrated by ultrafiltration, and purified by three liquid chromatography steps; one column of anion exchanger, one column of gel filtration, and again one column of anion exchanger. After re-equilibration of the purified viral suspension with Medium M-199 and adjustment of the antigen titer, the monovalent viral suspensions are inactivated at +37°C for at least 12 days with 1:4000 formalin.

Each dose (0.5 mL) of trivalent vaccine is formulated to contain 40 D antigen units of Type 1, 8 D antigen units of Type 2, and 32 D antigen units of Type 3 poliovirus. For each lot of IPOL vaccine, D-antigen content is determined in vitro using the D-antigen ELISA assay. IPOL vaccine is produced from vaccine concentrates diluted with M-199 medium. Also present are 0.5% of 2-phenoxyethanol and a maximum of 0.02% of formaldehyde per dose as preservatives. Neomycin, streptomycin, and polymyxin B are used in vaccine production; and, although purification procedures eliminate measurable amounts, less than 5 ng neomycin, 200 ng streptomycin, and 25 ng polymyxin B per dose may still be present. The residual calf bovine serum albumin is less than 50 ng/dose in the final vaccine.

The vaccine is clear and colorless and should be administered intramuscularly or subcutaneously.

The vial stopper is not made with natural rubber latex.

CLINICAL PHARMACOLOGY

Poliomyelitis is caused by poliovirus Types 1, 2, or 3. It is primarily spread by the fecal-oral route of transmission but may also be spread by the pharyngeal route.

Approximately 90% to 95% of poliovirus infections are asymptomatic. Nonspecific illness with low-grade fever and sore throat (minor illness) occurs in 4% to 8% of infections. Aseptic meningitis occurs in 1% to 5% of patients a few days after the minor illness has resolved. Rapid onset of asymmetric acute flaccid paralysis occurs in 0.1% to 2% of infections, and residual paralytic disease involving motor neurons (paralytic poliomyelitis) occurs in approximately 1 per 1,000 infections. (5)

Prior to the introduction of inactivated poliovirus vaccines in 1955, large outbreaks of poliomyelitis occurred each year in the United States (US). The annual incidence of paralytic disease of 11.4 cases/100,000 population declined to 0.5 cases by the time oral poliovirus vaccine (OPV) was introduced in 1961. Incidence continued to decline thereafter to a rate of 0.002 to 0.005 cases per 100,000 population. Of the 127 cases of paralytic poliomyelitis reported in the US between 1980 and 1994, six were imported cases (caused by wild polioviruses), two were "indeterminate" cases, and 119 were vaccine associated paralytic poliomyelitis (VAPP) cases associated with the use of live, attenuated oral poliovirus vaccine (OPV). (6) An all IPV schedule was adopted in 1999 to eliminate VAPP cases. (7)

Poliovirus Vaccine Inactivated induces the production of neutralizing antibodies against each type of virus which are related to protective efficacy. Antibody response in most children was induced after receiving fewer doses (8) of IPV vaccine than the vaccine available in the United States prior to 1988.

Studies in developed (8) and developing (9), (10) countries with a similar enhanced IPV manufactured by the same process as IPOL vaccine in primary monkey kidney cells have shown a direct relationship exists between the antigenic content of the vaccine, the frequency of seroconversion, and resulting antibody titer. Approval in the US was based upon demonstration of immunogenicity and safety in US children. (11)

In the US, 219 infants received three doses of a similar enhanced IPV at two, four, and eighteen months of age manufactured by the same process as IPOL vaccine except the cell substrate for IPV was using primary monkey kidney cells. Seroconversion to all three types of poliovirus was demonstrated in 99% of these infants after two doses of vaccine given at 2 and 4 months of age. Following the third dose of vaccine at 18 months of age, neutralizing antibodies were present at a level of ≥1:10 in 99.1% of children to Type 1 and 100% of children to Types 2 and 3 polioviruses. (3)

IPOL vaccine was administered to more than 700 infants between 2 to 18 months of age during three clinical studies conducted in the US using IPV only schedules and sequential IPV-OPV schedules. (12) (13) Seroprevalence rates for detectable serum neutralizing antibody (DA) at a ≥1:4 dilution were 95% to 100% (Type 1); 97% to 100% (Type 2) and 96% to 100% (Type 3) after two doses of IPOL vaccine depending on studies.

Table 1: US Studies with IPOL Vaccine Administered Using IPV Only or Sequential IPV-OPV Schedules
Age (months) for |  |  |  | Post Dose 2 |  |  |  | Post Dose 3 |  |  |  | Pre Booster |  |  |  | Post Booster
2 | 4 | 6 | 12 to 18 |  | Type 1 | Type 2 | Type 3 |  | Type 1 | Type 2 | Type 3 |  | Type 1 | Type 2 | Type 3 |  | Type 1 | Type 2 | Type 3
Dose 1 | Dose 2 | Dose 3 | Booster | N [N = Number of children from whom serum was available] | %DA [Detectable antibody (neutralizing titer ≥1:4)] | %DA | %DA | N | %DA | %DA | %DA | N | %DA | %DA | %DA | N | %DA | %DA | %DA
STUDY 1 (11) [IPOL vaccine given subcutaneously]
I(s) | I(s) | NA [NA – No poliovirus vaccine administered] | I(s) | 56 | 97 | 100 | 97 |  | – | – | – | 53 | 91 | 97 | 93 | 53 | 97 | 100 | 100
O | O | NA | O | 22 | 100 | 100 | 100 |  | – | – | – | 22 | 78 | 91 | 78 | 20 | 100 | 100 | 100
I(s) | O | NA | O | 17 | 95 | 100 | 95 |  | – | – | – | 17 | 95 | 100 | 95 | 17 | 100 | 100 | 100
I(s) | I(s) | NA | O | 17 | 100 | 100 | 100 |  | – | – | – | 16 | 100 | 100 | 94 | 16 | 100 | 100 | 100
STUDY 2 (10) [IPOL vaccine given intramuscularly]
I(c) | I(c) | NA | I(s) | 94 | 98 | 97 | 96 |  | – | – | – | 100 | 92 | 95 | 88 | 97 | 100 | 100 | 100
I(s) | I(s) | NA | I(s) | 68 | 99 | 100 | 99 |  | – | – | – | 72 | 100 | 100 | 94 | 75 | 100 | 100 | 100
I(c) | I(c) | NA | O | 75 | 95 | 99 | 96 |  | – | – | – | 77 | 86 | 97 | 82 | 78 | 100 | 100 | 97
I(s) | I(s) | NA | O | 101 | 99 | 99 | 95 |  | – | – | – | 103 | 99 | 97 | 89 | 107 | 100 | 100 | 100
STUDY 3 (10)
I(c) | I(c) | I(c) | O | 91 | 98 | 99 | 100 | 91 | 100 | 100 | 100 | 41 | 100 | 100 | 100 | 40 | 100 | 100 | 100
I(c) | I(c) | O | O | 96 | 100 | 98 | 99 | 94 | 100 | 100 | 99 | 47 | 100 | 100 | 100 | 45 | 100 | 100 | 100
I(c) | I(c) | I(c) + O | O | 91 | 96 | 97 | 100 | 85 | 100 | 100 | 100 | 47 | 100 | 100 | 100 | 46 | 100 | 100 | 100
I IPOL vaccine given either separately in association with DTP in two sites (s) or combined (c) with DTP in a dual chambered syringe
O OPV

In one study, (13) the persistence of DA in infants receiving two doses of IPOL vaccine at 2 and 4 months of age was 91% to 100% (Type 1), 97% to 100% (Type 2), and 93% to 94% (Type 3) at twelve months of age. In another study, (12) 86% to 100% (Type 1), 95% to 100% (Type 2), and 82% to 94% (Type 3) of infants still had DA at 18 months of age.

In trials and field studies conducted outside the US, IPOL vaccine, or a combination vaccine containing IPOL vaccine and DTP, was administered to more than 3,000 infants between 2 to 18 months of age using IPV only schedules and immunogenicity data are available from 1,485 infants. After two doses of vaccine given during the first year of life, seroprevalence rates for detectable serum neutralizing antibody (neutralizing titer ≥1:4) were 88% to 100% (Type 1); 84% to 100% (Type 2) and 94% to 100% (Type 3) of infants, depending on studies. When three doses were given during the first year of life, post-dose 3 DA ranged between 93% to 100% (Type 1); 89% to 100% (Type 2) and 97% to 100% (Type 3) and reached 100% for Types 1, 2, and 3 after the fourth dose given during the second year of life (12 to 18 months of age). (14)

In infants immunized with three doses of an unlicensed combination vaccine containing IPOL vaccine and DTP given during the first year of life, and a fourth dose given during the second year of life, the persistence of detectable neutralizing antibodies was 96%, 96%, and 97% against poliovirus Types 1, 2, and 3, respectively, at six years of age. DA reached 100% for all types after a booster dose of IPOL vaccine combined with DTP vaccine. (11) A survey of Swedish children and young adults given a Swedish IPV only schedule demonstrated persistence of detectable serum neutralizing antibody for at least 10 years to all three types of poliovirus. (15)

IPV is able to induce secretory antibody (IgA) produced in the pharynx and gut and reduces pharyngeal excretion of poliovirus Type 1 from 75% in children with neutralizing antibodies at levels less than 1:8 to 25% in children with neutralizing antibodies at levels more than 1:64. (4) (14) (16) (17) (18) (19) (20) (21) (22) There is also evidence of induction of herd immunity with IPV, (15) (23) (24) (25) (26) and that this herd immunity is sufficiently maintained in a population vaccinated only with IPV. (26)

VAPP has not been reported in association with administration of IPOL vaccine. (27) It is expected that an IPV only schedule will eliminate the risk of VAPP in both recipients and contacts compared to a schedule that included OPV. (7)

INDICATIONS AND USAGE

IPOL vaccine is indicated for active immunization of infants (as young as 6 weeks of age), children, and adults for the prevention of poliomyelitis caused by poliovirus Types 1, 2, and 3. (28)

INFANTS, CHILDREN AND ADOLESCENTS

General Recommendations

It is recommended that all infants (as young as 6 weeks of age), unimmunized children, and adolescents not previously immunized be vaccinated routinely against paralytic poliomyelitis. (29) Following the eradication of poliomyelitis caused by wild poliovirus from the Western Hemisphere (including North and South America) (30), an IPV-only schedule was recommended to eliminate VAPP. (7)

All children should receive four doses of IPV at ages 2, 4, 6 to 18 months, and 4 to 6 years. OPV is no longer available in the US and is not recommended for routine immunization. (7)

Previous clinical poliomyelitis (usually due to only a single poliovirus type) or incomplete immunization with OPV are not contraindications to completing the primary series of immunization with IPOL vaccine.

Children Incompletely Immunized

Children of all ages should have their immunization status reviewed and be considered for supplemental immunization as follows for adults. Time intervals between doses longer than those recommended for routine primary immunization do not necessitate additional doses as long as a final total of four doses is reached (see DOSAGE AND ADMINISTRATION section).

ADULTS

General Recommendations

Routine primary poliovirus vaccination of adults (generally those 18 years of age or older) residing in the US is not recommended. Unimmunized adults who are potentially exposed to wild poliovirus and have not been adequately immunized should receive polio vaccination in accordance with the schedule given in the DOSAGE AND ADMINISTRATION section. (28)

Persons with previous wild poliovirus disease who are incompletely immunized or unimmunized should be given additional doses of IPOL vaccine if they fall into one or more categories listed.

The following categories of adults are at an increased risk of exposure to wild polioviruses: (28) (31)

- Travelers to regions or countries where poliomyelitis is endemic or epidemic.
- Healthcare workers in close contact with patients who may be excreting polioviruses.
- Laboratory workers handling specimens that may contain polioviruses.
- Members of communities or specific population groups with disease caused by wild polioviruses.

IMMUNODEFICIENCY AND ALTERED IMMUNE STATUS

IPOL vaccine should be used in all patients with immunodeficiency diseases and members of such patients' households when vaccination of such persons is indicated. This includes patients with asymptomatic HIV infection, AIDS or AIDS-Related Complex, severe combined immunodeficiency, hypogammaglobulinemia, or agammaglobulinemia; altered immune states due to diseases such as leukemia, lymphoma, or generalized malignancy; or an immune system compromised by treatment with corticosteroids, alkylating drugs, antimetabolites or radiation. Immunogenicity of IPOL vaccine in individuals receiving immunoglobulin could be impaired, and patients with an altered immune state may or may not develop a protective response against paralytic poliomyelitis after administration of IPV. (32)

As with any vaccine, vaccination with IPOL vaccine may not protect 100% of individuals.

Use with other vaccines: refer to DOSAGE AND ADMINISTRATION section for this information.

CONTRAINDICATIONS

IPOL vaccine is contraindicated in persons with a history of hypersensitivity to any component of the vaccine, including 2-phenoxyethanol, formaldehyde, neomycin, streptomycin, and polymyxin B.

No further doses should be given if anaphylaxis or anaphylactic shock occurs within 24 hours of administration of one dose of vaccine.

Vaccination of persons with an acute, febrile illness should be deferred until after recovery; however, minor illness, such as mild upper respiratory infection, with or without low grade fever, are not reasons for postponing vaccine administration.

WARNINGS

Neomycin, streptomycin, polymyxin B, 2-phenoxyethanol, and formaldehyde are used in the production of this vaccine. Although purification procedures eliminate measurable amounts of these substances, traces may be present (see DESCRIPTION section), and allergic reactions may occur in persons sensitive to these substances (see CONTRAINDICATIONS section).

Systemic adverse reactions reported in infants receiving IPV concomitantly at separate sites or combined with DTP have been similar to those associated with administration of DTP alone. (11) Local reactions are usually mild and transient in nature.

Although no causal relationship between IPOL vaccine and Guillain-Barré Syndrome (GBS) has been established, (28) GBS has been temporally related to administration of another inactivated poliovirus vaccine. Deaths have been reported in temporal association with the administration of IPV (see ADVERSE REACTIONS section).

PRECAUTIONS

GENERAL

Prior to an injection of any vaccine, all known precautions should be taken to prevent adverse reactions. This includes a review of the patient's history with respect to possible sensitivity to the vaccine or similar vaccines.

Healthcare providers should question the patient, parent or guardian about reactions to a previous dose of this product, or similar product.

Epinephrine injection (1:1000) and other appropriate agents should be available to control immediate allergic reactions.

Healthcare providers should obtain the previous immunization history of the vaccinee, and inquire about the current health status of the vaccinee.

Immunodeficient patients or patients under immunosuppressive therapy may not develop a protective immune response against paralytic poliomyelitis after administration of IPV.

Administration of IPOL vaccine is not contraindicated in individuals infected with HIV. (33) (34) (35)

Special care should be taken to ensure that the injection does not enter a blood vessel.

Syncope (fainting) has been reported following vaccination with IPOL. Procedures should be in place to avoid injury from fainting.

INFORMATION FOR PATIENTS

Patients, parents, or guardians should be instructed to report any serious adverse reactions to their healthcare provider.

The healthcare provider should inform the patient, parent, or guardian of the benefits and risks of the vaccine.

The healthcare provider should inform the patient, parent, or guardian of the importance of completing the immunization series.

The healthcare provider should provide the Vaccine Information Statements (VISs) which are required to be given with each immunization.

DRUG INTERACTIONS

There are no known interactions of IPOL vaccine with drugs or foods. Concomitant administration of other parenteral vaccines, with separate syringes at separate sites, is not contraindicated. The first two doses of IPOL vaccine may be administered at separate sites using separate syringes concomitantly with DTaP, acellular pertussis, Haemophilus influenzae type b (Hib), and hepatitis B vaccines. From historical data on the antibody responses to diphtheria, tetanus, acellular pertussis, Hib, or hepatitis B vaccines used concomitantly or in combination with IPOL vaccine, no interferences have been observed on the immunological end points accepted for clinical protection. (11) (16) (36) (See DOSAGE AND ADMINISTRATION section.)

If IPOL vaccine has been administered to persons receiving immunosuppressive therapy, an adequate immunologic response may not be obtained. (See PRECAUTIONS – GENERAL section.)

CARCINOGENESIS, MUTAGENESIS, IMPAIRMENT OF FERTILITY

Long-term studies in animals to evaluate carcinogenic potential or impairment of fertility have not been conducted.

PREGNANCY

Animal reproduction studies have not been conducted with IPOL vaccine. It is also not known whether IPOL vaccine can cause fetal harm when administered to a pregnant woman or can affect reproduction capacity. IPOL vaccine should be given to a pregnant woman only if clearly needed.

NURSING MOTHERS

It is not known whether IPOL vaccine is excreted in human milk. Because many drugs are excreted in human milk, caution should be exercised when IPOL vaccine is administered to a nursing woman.

PEDIATRIC USE

SAFETY AND EFFECTIVENESS OF IPOL VACCINE IN INFANTS BELOW SIX WEEKS OF AGE HAVE NOT BEEN ESTABLISHED. (12) (20) (See DOSAGE AND ADMINISTRATION section.)

In the US, infants receiving two doses of IPV at 2 and 4 months of age, the seroprevalence to all three types of poliovirus was demonstrated in 95% to 100% of these infants after two doses of vaccine. (12) (13)

ADVERSE REACTIONS

Body System As A Whole

In earlier studies with the vaccine grown in primary monkey kidney cells, transient local reactions at the site of injection were observed. (3) Erythema, induration and pain occurred in 3.2%, 1% and 13%, respectively, of vaccinees within 48 hours post-vaccination. Temperatures of ≥39°C (≥102°F) were reported in 38% of vaccinees. Other symptoms included irritability, sleepiness, fussiness, and crying. Because IPV was given in a different site but concurrently with Diphtheria and Tetanus Toxoids and Pertussis Vaccine Adsorbed (DTP), these systemic reactions could not be attributed to a specific vaccine. However, these systemic reactions were comparable in frequency and severity to that reported for DTP given alone without IPV. (12) Although no causal relationship has been established, deaths have occurred in temporal association after vaccination of infants with IPV. (37)

Four additional US studies using IPOL vaccine in more than 1,300 infants, (12) between 2 to 18 months of age administered with DTP at the same time at separate sites or combined have demonstrated that local and systemic reactions were similar when DTP was given alone.

Table 2 (12): Percentage of Infants Presenting with Local or Systemic Reactions at 6, 24, and 48 Hours of Immunization with IPOL Vaccine Administered Intramuscularly Concomitantly at Separate Sites with Sanofi [Sanofi Pasteur Inc. formerly known as Aventis Pasteur Inc.] Whole-Cell DTP Vaccine at 2 and 4 Months of Age and with Sanofi Acellular Pertussis Vaccine (Tripedia®) at 18 Months of Age
 | AGE AT IMMUNIZATION
REACTION | 2 Months (n=211) |  |  | 4 Months (n=206) |  |  | 18 Months [Children who have been vaccinated with Tripedia vaccine.] (n=74)
REACTION | 6 Hrs. | 24 Hrs. | 48 Hrs. | 6 Hrs. | 24 Hrs. | 48 Hrs. | 6 Hrs. | 24 Hrs. | 48 Hrs.
Local, IPOL vaccine alone [Data are from the IPOL vaccine administration site, given intramuscularly.]
Erythema >1" | 0.5% | 0.5% | 0.5% | 1.0% | 0.0% | 0.0% | 1.4% | 0.0% | 0.0%
Swelling | 11.4% | 5.7% | 0.9% | 11.2% | 4.9% | 1.9% | 2.7% | 0.0% | 0.0%
Tenderness | 29.4% | 8.5% | 2.8% | 22.8% | 4.4% | 1.0% | 13.5% | 4.1% | 0.0%
Systemic [The adverse reaction profile includes the concomitant use of Sanofi whole-cell DTP vaccine or Tripedia vaccine with IPOL vaccine. Rates are comparable in frequency and severity to that reported for whole-cell DTP given alone.]
Fever >102.2°F | 1.0% | 0.5% | 0.5% | 2.0% | 0.5% | 0.0% | 0.0% | 0.0% | 4.2%
Irritability | 64.5% | 24.6% | 17.5% | 49.5% | 25.7% | 11.7% | 14.7% | 6.7% | 8.0%
Tiredness | 60.7% | 31.8% | 7.1% | 38.8% | 18.4% | 6.3% | 9.3% | 5.3% | 4.0%
Anorexia | 16.6% | 8.1% | 4.3% | 6.3% | 4.4% | 2.4% | 2.7% | 1.3% | 2.7%
Vomiting | 1.9% | 2.8% | 2.8% | 1.9% | 1.5% | 1.0% | 1.3% | 1.3% | 0.0%
Persistent Crying | Percentage of infants within 72 hours after immunization was 0.0% after dose one, 1.4% after dose two, and 0.0% after dose three.

Digestive System

Anorexia and vomiting occurred with frequencies not significantly different as reported when DTP was given alone without IPV or OPV. (12)

Nervous System

Although no causal relationship between IPOL vaccine and GBS has been established, (28) GBS has been temporally related to administration of another inactivated poliovirus vaccine.

Post-marketing Experience

The following adverse events have been identified during postapproval use of IPOL vaccine. Because these events are reported voluntarily from a population of uncertain size, it may not be possible to reliably estimate their frequency or establish a causal relationship to vaccine exposure. Adverse events were included based on one or more of the following factors: severity, frequency of reporting or strength of evidence for a causal relationship.

- Blood and lymphatic system disorders: lymphadenopathy
- General disorders and administration site conditions: agitation, injection site reaction including injection site rash and mass
- Immune system disorders: type I hypersensitivity including allergic reaction, anaphylactic reaction, and anaphylactic shock
- Musculoskeletal and connective tissue disorders: arthralgia, myalgia
- Nervous system disorders: convulsion, febrile convulsion, headache, paresthesia, somnolence, syncope
- Skin and subcutaneous tissue disorders: rash, urticaria

Reporting of Adverse Events

The National Vaccine Injury Compensation Program, established by the National Childhood Vaccine Injury Act of 1986, requires physicians and other healthcare providers who administer vaccines to maintain permanent vaccination records and to report occurrences of certain adverse events to the US Department of Health and Human Services. Reportable events include those listed in the Act for each vaccine and events specified in the package insert as contraindications to further doses of that vaccine. (38) (39) (40)

Reporting by parents or guardians of all adverse events after vaccine administration should be encouraged. Adverse events following immunization with vaccine should be reported by healthcare providers to the US Department of Health and Human Services (DHHS) Vaccine Adverse Event Reporting System (VAERS). Reporting forms and information about reporting requirements or completion of the form can be obtained from VAERS through a toll-free number 1-800-822-7967. (38) (39) (40)

Healthcare providers also should report these events to the Pharmacovigilance Department, Sanofi Pasteur Inc., Discovery Drive, Swiftwater, PA 18370 or call 1-800-822-2463.

DOSAGE AND ADMINISTRATION

Parenteral drug products should be inspected visually for particulate matter and discoloration prior to administration, whenever solution and container permit. The vial and its packaging should be inspected prior to use for evidence of leakage or a faulty seal. If evidence of such defects are observed, the vaccine should not be used. Do not remove the vial stopper or the metal seal holding it in place.

After preparation of the injection site, using a suitable sterile needle and aseptic technique, immediately administer IPOL vaccine intramuscularly or subcutaneously. In infants and small children, the mid-lateral aspect of the thigh is the preferred site. In older children and adults, IPOL vaccine should be administered intramuscularly or subcutaneously in the deltoid area. IPOL should not be combined through reconstitution or mixed with any other vaccine.

To help avoid HIV (AIDS), HBV (Hepatitis), and other infectious diseases due to accidental needlesticks, contaminated needles should not be recapped or removed, unless there is no alternative or that such action is required by a specific medical procedure.

Care should be taken to avoid administering the injection into or near blood vessels and nerves. If blood or any suspicious discoloration appears in the syringe, do not inject but discard contents and repeat procedures using a new dose of vaccine administered at a different site.

DO NOT ADMINISTER VACCINE INTRAVENOUSLY.

Children

The primary series of IPOL vaccine consists of three 0.5 mL doses administered intramuscularly or subcutaneously, preferably eight or more weeks apart and usually at ages 2, 4, and 6 to 18 months. Under no circumstances should the vaccine be given more frequently than four weeks apart. The first immunization may be administered as early as six weeks of age. For this series, a booster dose of IPOL vaccine is administered at 4 to 6 years of age. (41)

Use with Other Vaccines

From historical data on the antibody responses to diphtheria, tetanus, whole-cell or acellular pertussis, Hib, or hepatitis B vaccines used concomitantly with IPOL vaccine, no interferences have been observed on the immunological end points accepted for clinical protection. (11) (16) (36) (See DRUG INTERACTIONS section.)

If the third dose of IPOL vaccine is given between 12 to 18 months of age, it may be desirable to administer this dose with Measles, Mumps, and Rubella (MMR) vaccine and/or other vaccines using separate syringes at separate sites, (28) but no data on the immunological interference between IPOL vaccine and these vaccines exist.

Use in Previously Vaccinated Children

Children and adolescents with a previously incomplete series of polio vaccine should receive sufficient additional doses of IPOL vaccine to complete the series.

Interruption of the recommended schedule with a delay between doses does not interfere with the final immunity. There is no need to start the series over again, regardless of the time elapsed between doses.

The need to routinely administer additional doses is unknown at this time. (28)

Adults

Unvaccinated Adults

A primary series of IPOL vaccine is recommended for unvaccinated adults at increased risk of exposure to poliovirus. While the responses of adults to primary series have not been studied, the recommended schedule for adults is two 0.5 mL doses given at a 1 to 2 month interval and a third 0.5 mL dose given 6 to 12 months later. If less than 3 months but more than 2 months are available before protection is needed, three doses of IPOL vaccine should be given at least 1 month apart. Likewise, if only 1 or 2 months are available, two 0.5 mL doses of IPOL vaccine should be given at least 1 month apart. If less than 1 month is available, a single 0.5 mL dose of IPOL vaccine is recommended. (28)

Incompletely Vaccinated Adults

Adults who are at an increased risk of exposure to poliovirus and who have had at least one dose of OPV, fewer than three doses of conventional IPV or a combination of conventional IPV or OPV totaling fewer than three doses should receive at least one 0.5 mL dose of IPOL vaccine. Additional doses needed to complete a primary series should be given if time permits. (28)

Completely Vaccinated Adults

Adults who are at an increased risk of exposure to poliovirus and who have previously completed a primary series with one or a combination of polio vaccines can be given a 0.5 mL dose of IPOL vaccine.

The preferred injection site of IPOL vaccine for adults is in the deltoid area.

HOW SUPPLIED

Multi-dose vial , 5mL: NDC 49281-860-78. Supplied as package: NDC 49281-860-10.

STORAGE

The vaccine is stable if stored in the refrigerator at 2°C to 8°C (35°F to 46°F). The vaccine must not be frozen.

Protect from light.

REFERENCES

1 van Wezel AL, et al. Inactivated poliovirus vaccine: Current production methods and new developments. Rev Infect Dis 6 (Suppl 2): S335-S340, 1984.
2 Montagnon BJ, et al. Industrial scale production of inactivated poliovirus vaccine prepared by culture of Vero cells on microcarrier. Rev Infect Dis 6 (Suppl 2): S341-S344, 1984.
3 McBean AM, et al. Serologic response to oral polio vaccine and enhanced-potency inactivated polio vaccines. Am J Epidemiol 128: 615-628, 1988.
4 Murdin AD, et al. Inactivated poliovirus vaccine: past and present experience. Vaccine 8: 735-746, 1996.
5 Sabin AB. Poliomyelitis. In Brande AI, Davis CE, Fierer J (eds) International Textbook of Medicine, Vol II. Infectious Diseases and Medical Microbiology. 2nd ed. Philadelphia, WB Saunders, 1986.
6 Prevots DR, et al. Vaccine-associated paralytic poliomyelitis in the United States, 1980-1994: current risk and potential impact of a proposed sequential schedule of IPV followed by OPV (Abstract #H90). In: Abstracts of the 36th Interscience Conference on Antimicrobial Agents and Chemotherapy. Washington, DC. American Society for Microbiology, 179, 1996.
7 ACIP. Updated Recommendations of the Advisory Committee on Immunization Practices. Poliomyelitis Prevention in the United States. MMWR 49: No. RR-5, 2000.
8 Salk J, et al. Antigen content of inactivated poliovirus vaccine for use in a one- or two-dose regimen. Ann Clin Res 14: 204-212, 1982.
9 Salk J, et al. Killed poliovirus antigen titration in humans. Develop Biol Standard 41: 119-132, 1978.
10 Salk J, et al. Theoretical and practical considerations in the application of killed poliovirus vaccine for the control of paralytic poliomyelitis. Develop Biol Standard 47: 181-198, 1981.
11 Unpublished data available from Sanofi Winthrop Industrie.
12 Unpublished data available from Sanofi Pasteur Inc.
13 Faden H, et al. Comparative evaluation of immunization with live attenuated and enhanced potency inactivated trivalent poliovirus vaccines in childhood: Systemic and local immune responses. J Infect Dis 162: 1291-1297, 1990.
14 Vidor E, et al. The place of DTP/eIPV vaccine in routine pædiatric vaccination. Rev Med Virol 4: 261-277, 1994.
15 Bottiger M. Long-term immunity following vaccination with killed poliovirus vaccine in Sweden, a country with no circulating poliovirus. Rev Infect Dis 6 (Suppl 2): S548-S551, 1984.
16 Plotkin SA, et al. Inactivated polio vaccine for the United States: a missed vaccination opportunity. Pediatr Infect Dis J 14: 835-839, 1995.
17 Marine WM, et al. Limitation of fecal and pharyngeal poliovirus excretion in Salk-vaccinated children. A family study during a Type 1 poliomyelitis epidemic. Amer J Hyg 76: 173-195, 1962.
18 Bottiger M, et al. Vaccination with attenuated Type 1 poliovirus, the Chat strain. II. Transmission of virus in relation to age. Acta Paed Scand 55: 416-421, 1966.
19 Dick GWA, et al. Vaccination against poliomyelitis with live virus vaccines. Effect of previous Salk vaccination on virus excretion. Brit Med J 2: 266-269, 1961.
20 Wehrle PF, et al. Transmission of poliovirus; III. Prevalence of polioviruses in pharyngeal secretions of infected household contacts of patients with clinical disease. Pediatrics 27: 762-764, 1961.
21 Adenyi-Jones SC, et al. Systemic and local immune responses to enhanced-potency inactivated poliovirus vaccine in premature and term infants. J Pediatr 120: No 5, 686-689, 1992.
22 Chin TDY. Immunity induced by inactivated poliovirus vaccine and excretion of virus. Rev Infect Dis 6 (Suppl 2): S369-S370, 1984.
23 Salk D. Herd effect and virus eradication with use of killed poliovirus vaccine. Develop Biol Standard 47: 247-255, 1981.
24 Bijerk H. Surveillance and control of poliomyelitis in the Netherlands. Rev Infect Dis 6 (Suppl 2): S451-S456, 1984.
25 Lapinleimu K. Elimination of poliomyelitis in Finland. Rev Infect Dis 6 (Suppl 2): S457-S460, 1984.
26 Conyn van Spaendonck M, et al. Circulation of Poliovirus during the poliomyelitis outbreak in the Netherlands in 1992-1993. Amer J Epidemiology 143: 929-935, 1996.
27 Strebel PM, et al. Epidemiology of poliomyelitis in the United States one decade after the last reported case of indigenous wild virus associated disease. Clin Infect Dis 14: 568-579, 1992.
28 ACIP. Poliomyelitis prevention in the United States: introduction of a sequential vaccination schedule of Inactivated Poliovirus Vaccine followed by Oral Poliovirus Vaccine. MMWR 46: No. RR-3, 1997.
29 WHO. Weekly Epidemiology Record 54: 82-83, 1979.
30 Certification of poliomyelitis eradication - the Americas, 1994. MMWR 43: 720-722, 1994.
31 Institute of Medicine. An evaluation of poliomyelitis vaccine poliomyelitis vaccine policy options. Washington, DC. National Academy of Sciences, 1988.
32 ACIP. Immunization of children infected with human T-lymphotropic virus type III/lymphadenopathy-associated virus. MMWR 35: 595-606, 1986.
33 ACIP. General recommendations on immunization. MMWR 43: No. RR-1, 1994.
34 Barbi M, et al. Antibody response to inactivated polio vaccine (eIPV) in children born to HIV positive mothers. Eur J Epidemiol 8: 211-216, 1992.
35 Varon D, et al. Response to hemophilic patients to poliovirus vaccination: Correlation with HIV serology and with immunological parameters. J Med Virol 40: 91-95, 1993.
36 Vidor E, et al. Fifteen-years experience with vero-produced enhanced potency inactivated poliovirus vaccine (eIPV). Ped Infect Dis J, 312-322, 1997.
37 Stratton, R. et al. Adverse Events Associated with Childhood Vaccines. Polio Vaccines. National Academy Press, 295-299, 1994.
38 CDC. Vaccine Adverse Event Reporting System - United States. MMWR 39: 730-733, 1990.
39 CDC. National Childhood Vaccine Injury Act. Requirements for permanent vaccination records and for reporting of selected events after vaccination. MMWR 37: 197-200, 1988.
40 Food & Drug Administration. New Reporting Requirements for Vaccine Adverse Events. FDA Drug Bull 18 (2), 16-18, 1988.
41 Recommended childhood immunization schedule - United States, 1999. MMWR 48: 12-16, 1999.

Product Information as of January 2026

Manufactured by:
Sanofi Winthrop Industrie
Marcy l'Etoile France
US Govt License #1724

Distributed by:
Sanofi Pasteur Inc.
Swiftwater PA 18370 USA
1-800-VACCINE (1-800-822-2463)

PRINCIPAL DISPLAY PANEL - 10 Dose Vial Label

multi-dose vial (10 DOSES)
IPV
Poliovirus Vaccine
Inactivated - IPOL®

Dosage: 0.5 mL IM or SC.
Rx only
See enclosed package insert.
Store at 2° to 8°C (35° to 46°F).
DO NOT FREEZE.

US Govt Lic #1724
Mfg by: Sanofi Pasteur SA,
Marcy L'Etoile France
Dist by: Sanofi Pasteur Inc.

PRINCIPAL DISPLAY PANEL - 10 Dose Vial Package

NDC 49281-860-10
IPV

multi-dose vial (10 DOSES)

Poliovirus Vaccine
Inactivated - IPOL®

FOR INTRAMUSCULAR OR SUBCUTANEOUS ADMINISTRATION.

Rx only

SANOFI PASTEUR